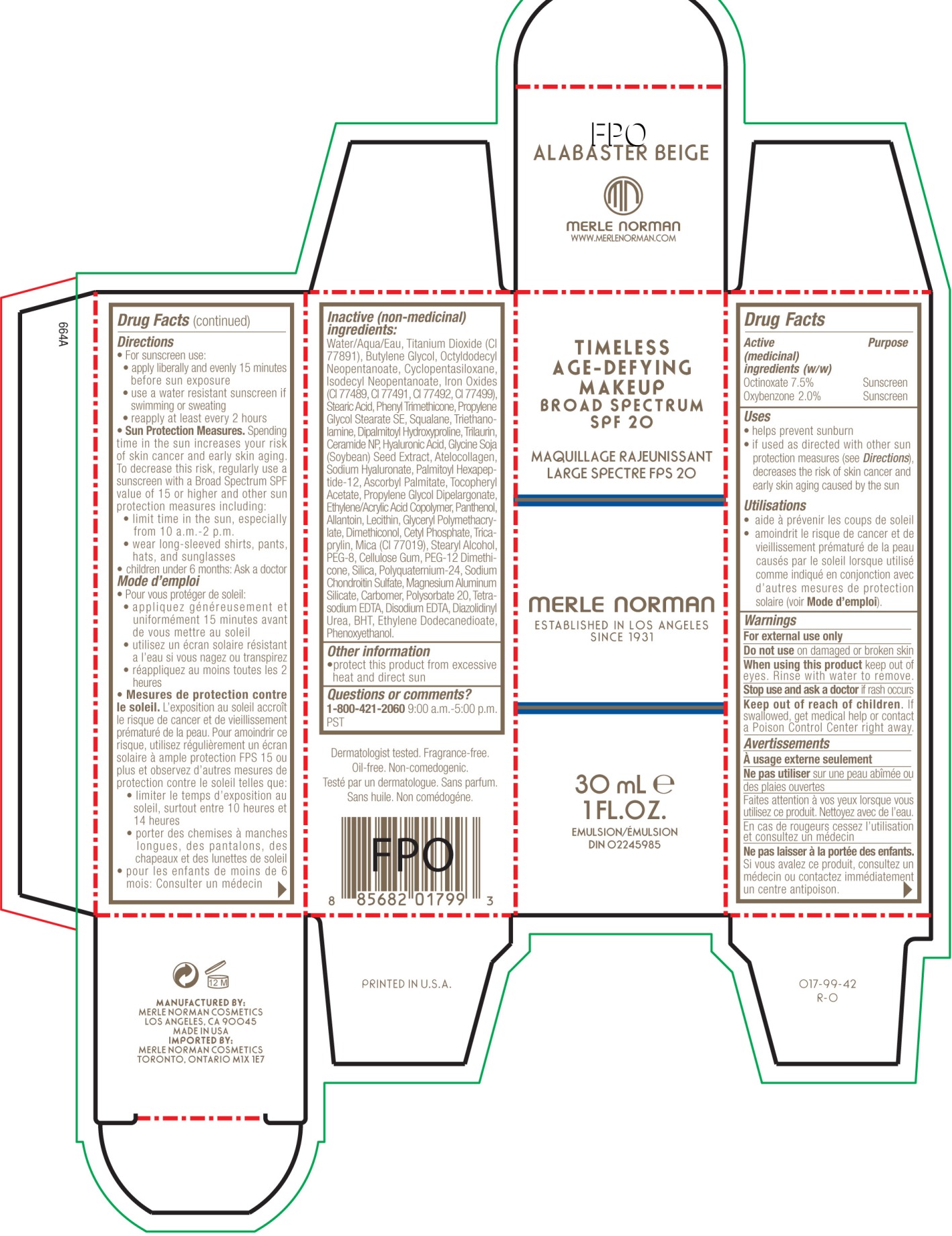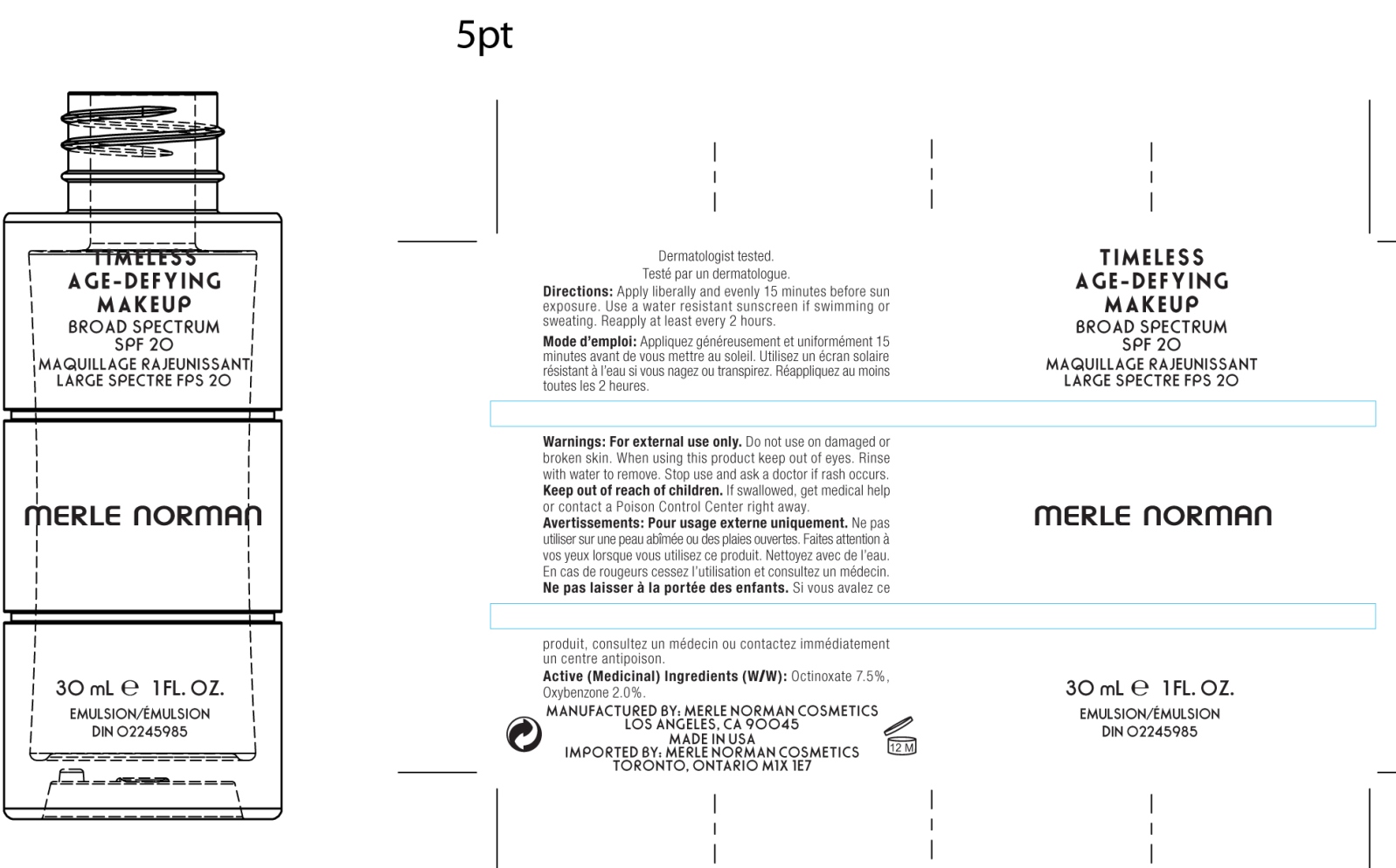 DRUG LABEL: Timeless Age Defying SPF 20
NDC: 57627-115 | Form: CREAM
Manufacturer: Merle Norman
Category: otc | Type: HUMAN OTC DRUG LABEL
Date: 20170123

ACTIVE INGREDIENTS: OCTINOXATE 2.25 g/30 mL; OXYBENZONE .6 g/30 mL
INACTIVE INGREDIENTS: TITANIUM DIOXIDE; BUTYLENE GLYCOL; ISODECYL NEOPENTANOATE; FERROUS OXIDE; FERRIC OXIDE RED; FERRIC OXIDE YELLOW; FERROSOFERRIC OXIDE; STEARIC ACID; PHENYL TRIMETHICONE; SQUALANE; TROLAMINE; DIPALMITOYL HYDROXYPROLINE; TRILAURIN; CERAMIDE 3; HYALURONIC ACID; SOYBEAN; HYALURONATE SODIUM; PALMITOYL OLIGOPEPTIDE; ASCORBYL PALMITATE; .ALPHA.-TOCOPHEROL ACETATE, D-; PANTHENOL; ALLANTOIN; CETYL PHOSPHATE; TRICAPRYLIN; MICA; STEARYL ALCOHOL; POLYETHYLENE GLYCOL 400; CARBOXYMETHYLCELLULOSE SODIUM; PEG-12 DIMETHICONE (300 CST); SILICON DIOXIDE; MAGNESIUM ALUMINUM SILICATE; POLYSORBATE 20; EDETATE SODIUM; EDETATE DISODIUM; DIAZOLIDINYL UREA; BUTYLATED HYDROXYTOLUENE

Timeless Age-Defying Makeup SPF 20

Active Ingredients purpose

Octinoxate 7.5% Sunscreen

Oxybenzone 2.0% Sunscreen

Uses
· helps prevent sunburn
· If used as directed with other sun protection measures (see Directions),
decreases the risk of skin cancer and early skin aging caused by the sun

Keep out of reach of children. If product is swallowed, get medical help or
contact a Poison Control Center right away.

Stop use and ask a doctor if rash occurs

Warnings

· For external use only
· Do not use on damaged or broken skin
· When using this product keep out of eyes. Rinse with water to remove.

Directions

For sunscreen use:

· Apply liberally 15 minutes before sun exposure

· Use a water resistant sunscreen if swimming or sweating

· Reapply at least every 2 hours

· Sun Protection Measures. Spending time in the sun increases your risk of skin
cancer and early skin aging. To decrease this risk, regularly use a sunscreen
with broad spectrum SPF of 15 or higher and other sun protection measures
including:
· limit time in the sun, especially from 10 a.m. - 2 p.m.
· wear long-sleeve shirts, pants, hats, and sunglasses
· Children under 6 months: Ask a doctor

INACTIVE INGREDIENT

Inactive ingredients: Water (Aqua), Titanium Dioxide, Butylene Glycol, Octldodecyl Neopentanoate, Cyclopentasoloxane, Isodecyl Neopentanoate, Iron Oxides, Stearic Acid, Phenyl Trimethicone, Propylene Glycol Stearate SE, Squalane, Triethanolamine, Dipalmitoyl Hydroxyproline, Trilaurin, Ceramide 3, Hyaluronic Acid, Glycine Soja, (Soybean) Seed Extract, Atelocollagen, Sodium Hyaluronate, Palmitoyl Oligopeptide, Ascorbyl Palmitate, Tocopheryl Acetate, Propylene Glycol Dipelargonate, Ethylene/ Acrylic Acid Copolymer, Panthenol, Allantoin, Lecithin, Glyceryl Polymethacrylate, Dimethionol, Cetyl Phosphate, Tricaprylin, Mica (Cl 77019), Stearyl Alcohol, PEG-8, Cellulose gum, PEG-12 Dimethicone, Silica, Polyquaternium-24, Sodium Chondroitin Sulfate, Magnesium Aluminum Silicate, Carbomer, Polysorbate 20, Tetrasodium EDTA, Disodium EDTA, Diazolidinyl Urea, BHT, Ethylene Dodecanedioate Phenoxyethanol

PACKAGE LABEL

Timeless

Age-Defying Makeup SPF 20

Merle Norman

30 mL 1 FL. OZ.